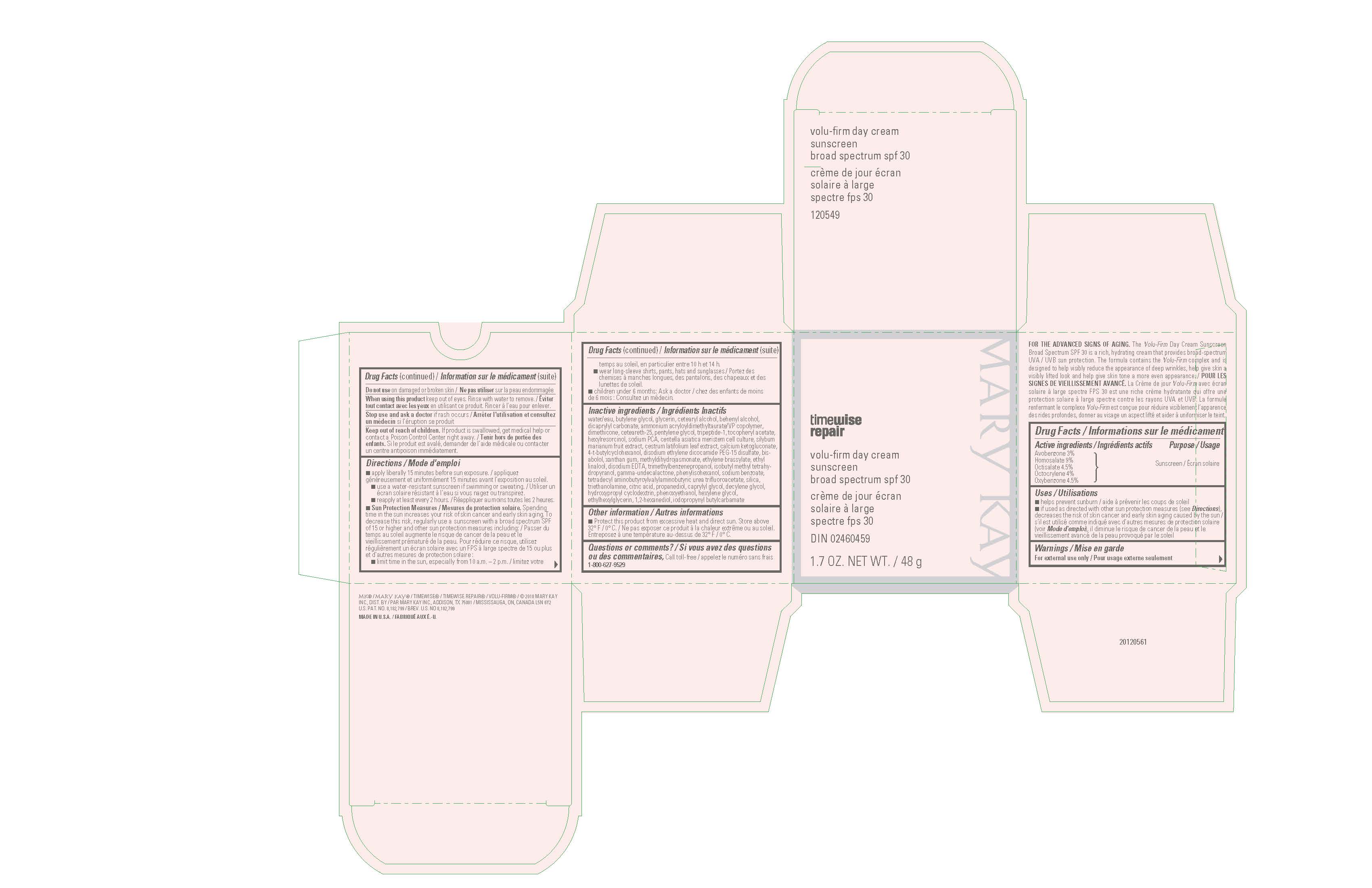 DRUG LABEL: Mary Kay TimeWise Repair Volu-Firm Day Cream Broad Spectrum SPF 30
NDC: 51531-0549 | Form: CREAM
Manufacturer: Mary Kay Inc.
Category: otc | Type: HUMAN OTC DRUG LABEL
Date: 20241217

ACTIVE INGREDIENTS: AVOBENZONE 3 g/100 g; HOMOSALATE 9 g/100 g; OCTISALATE 4.5 g/100 g; OCTOCRYLENE 4 g/100 g; OXYBENZONE 4.5 g/100 g
INACTIVE INGREDIENTS: WATER; BUTYLENE GLYCOL; GLYCERIN; CETOSTEARYL ALCOHOL; DOCOSANOL; DICAPRYLYL CARBONATE; AMMONIUM ACRYLOYLDIMETHYLTAURATE/VP COPOLYMER; DIMETHICONE; CETEARETH-25; PENTYLENE GLYCOL; PHENOXYETHANOL; METHYL DIHYDROJASMONATE (SYNTHETIC); DISODIUM ETHYLENE DICOCAMIDE PEG-15 DISULFATE; CALCIUM 2-KETOGLUCONATE; HEXYLRESORCINOL; 4-TERT-BUTYLCYCLOHEXANOL; SILICON DIOXIDE; ETHYLENE BRASSYLATE; CAPRYLYL GLYCOL; EDETATE DISODIUM; ETHYL LINALOOL; TROLAMINE; LEVOMENOL; DECYLENE GLYCOL; .ALPHA.-TOCOPHEROL ACETATE; HYDROXYPROPYL .ALPHA.-CYCLODEXTRIN; 1,2-HEXANEDIOL; CENTELLA ASIATICA; ETHYLHEXYLGLYCERIN; HEXYLENE GLYCOL; SODIUM PYRROLIDONE CARBOXYLATE; TRIMETHYLBENZENEPROPANOL; 2-ISOBUTYL-4-METHYLTETRAHYDROPYRAN-4-OL; MILK THISTLE; .GAMMA.-UNDECALACTONE; CITRIC ACID MONOHYDRATE; PHENYLISOHEXANOL; PROPANEDIOL; IODOPROPYNYL BUTYLCARBAMATE; CESTRUM LATIFOLIUM LEAF; XANTHAN GUM; SODIUM BENZOATE; TETRADECYL AMINOBUTYROYLVALYLAMINOBUTYRIC UREA TRIFLUOROACETATE; PREZATIDE; MAGNESIUM CHLORIDE

Mary Kay TimeWise Repair VoluFirm Day Cream SPF 30 (2018 update)
Drug Facts

Active Ingredients

Avobenzone 3%

Homosalate 9%

Octisalate 4.5%

Octocrylene 4%

Oxybenzone 4.5%

Purpose

Sunscreen

Uses

- helps prevent sunburn
- if used as directed with other sun protection measures (see Directions), decreases the risk of skin cancer and early skin aging caused by the sun

Warnings

For external use only

Do not use

on damaged or broken skin

When using this product

keep out of eyes. Rinse with water to remove.

Stop use and ask a doctor

if rash occurs

Keep out of reach of children.

If product is swallowed, get medical help or contact a Poison Control Center right away.

Directions

- apply liberally 15 minutes before sun exposure
- use a water-resistant sunscreen if swimming or sweating
- reapply at least every 2 hours
- Sun Protection Measures. Spending time in the sun increases your risk of skin cancer and early skin aging. To decrease this risk, regularly use a sunscreen with a broad spectrum SPF of 15 or higher and other sun protection measures including:
- limit time in the sun, especially from 10 a.m. - 2 p.m.
- wear long-sleeve shirts, pants, hats, and sunglasses
- children under 6 months: Ask a doctor

Inactive ingredients

water, butylene glycol, glycerin, cetearyl alcohol, behenyl alcohol, dicaprylyl carbonate, ammonium acryloyldimethyltaurate/VP copolymer, dimethicone, ceteareth-25, pentylene glycol, tripeptide-1, tocopheryl acetate, hexylresorcinol, sodium PCA, centella asiatica meristem cell culture, silybum marianum fruit extract, cestrum latifolium leaf extract, calcium ketogluconate, 4-t-butylcyclohexanol, disodium ethylene dicocamide PEG-15 disulfate, bisabolol, xanthan gum, methyldihydrojasmonate, ethylene brassylate, ethyl linalool, disodium EDTA, trimethylbenzenepropanol, isobutyl methyl tetrahydropyranol, gamma-undecalactone, phenylisohexanol, sodium benzoate, tetradecyl aminobutyroylvalylaminobutyric urea trifuoroacetate, silica, triethanolamine, citric acid, propanediol, caprylyl glycol, decylene glycol, hydroxypropyl cyclodextrin, phenoxyethanol, hexylene glycol, ethylhexylglycerin, 1,2-hexanediol, magnesium chloride, iodopropynyl butylcarbamate

Other information

- protect this product from excessive heat and direct sun. Store above 32° F / 0° C.

Questions or comments?

Call toll free 1-800-627-9529

Principal Display Panel - 48 g carton

Mary Kay

timewise repair

volu-firm day cream

sunscreen

broad spectrum

spf 30

1.7 OZ. NET WT. / 48 g